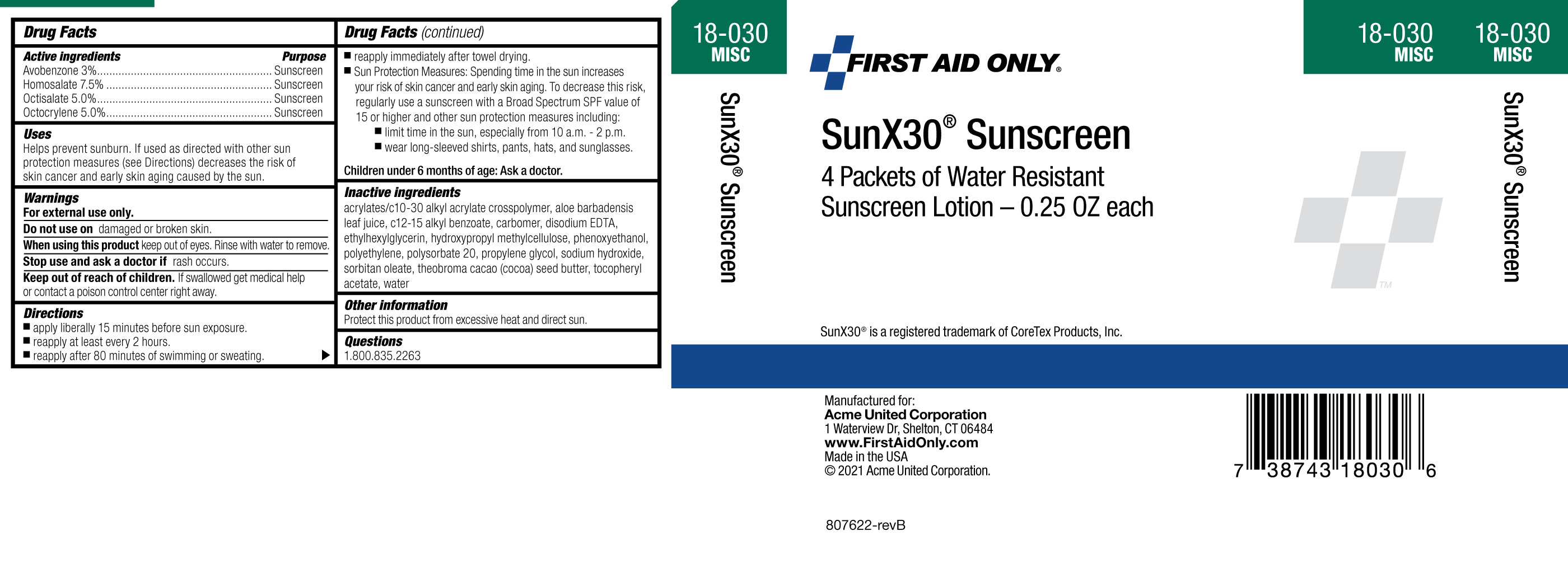 DRUG LABEL: First Aid Only SunX30 Sunscreen
NDC: 0924-0802 | Form: LOTION
Manufacturer: Acme United Corporation
Category: otc | Type: HUMAN OTC DRUG LABEL
Date: 20241018

ACTIVE INGREDIENTS: OCTOCRYLENE 5 g/100 mL; AVOBENZONE 3 g/100 mL; HOMOSALATE 7.5 g/100 mL; OCTISALATE 5 g/100 mL
INACTIVE INGREDIENTS: ALKYL (C12-15) BENZOATE; CARBOMER HOMOPOLYMER, UNSPECIFIED TYPE; DISODIUM EDTA-COPPER; SODIUM HYDROXIDE; PEG-6 SORBITAN OLEATE; THEOBROMA CACAO WHOLE; ETHYLHEXYLGLYCERIN; POLYSORBATE 20; METHYLCELLULOSE, UNSPECIFIED; PROPYLENE GLYCOL PROPYL ETHER; MEDIUM DENSITY POLYETHYLENE; WATER; ALOE VERA LEAF; .ALPHA.-TOCOPHEROL ACETATE; PHENOXYETHANOL; ACRYLATES CROSSPOLYMER-6

First Aid Only SunX30 Sunscreen Lotion

Active ingredients

Avobenzone 3%

Homosalate 7.5%

Octisalate 5%

Octocylene 5%

Purpose

Sunscreen

Sunscreen

Sunscreen

Sunscreen

Warnings

For external use only

Do not use

on damaged or broken skin

When using this product

keep out of the eyes. Rinse with water to remove

Stop use and ask a doctor

if rash occurs

Keep out of the reach of children.

If product is swallowed, get medical help or contact a Poison Control Center right away.

Uses

- helps prevent sunburn
- if used as directed with other sun protection measures (see Directions), decreases the risk of skin cancer and early skin aging caused by the sun.

Directions

- apply liberally 15 minutes before sun exposure
- reapply:
- after 80 minutes of swimming or sweating
  - immediately after towel drying
  - at least every 2 hours

Sun Protection Measures. Spending time in the sun increases your risk of skin cancer and early skin aging. To decrease this risk, regularly use a sunscreen with a broad spectrum SPF of 15 or higher and other sun protection measures including:

- limit time in the sun, especially from 10:00 a.m. - 2 p.m.
- wear long-sleeved shirts, pants, hats and sunglasses.

Children under 6 months: Ask a doctor

Other information

- Protect this product from excessive heat or direct sun.

Inactive ingredients

acrylates/C10-30 alkyl acrylate crosspolymer, aloe barbadensis leaf juice, C12-15 alkyl benzoate, carbomer, disodium EDTA, ethylhexylglycerin, hydroxypropyl methylcellulose, phenoxyethanol, polyethylene, polysorbate 20, propylene glycol, sodium hydroxide, sorbitan, oleate, theobroma cacao (cocoa) seed butter, tocopherol acetate, water

Questions

1-800-835-2263

PACKAGE LABEL

carton Image